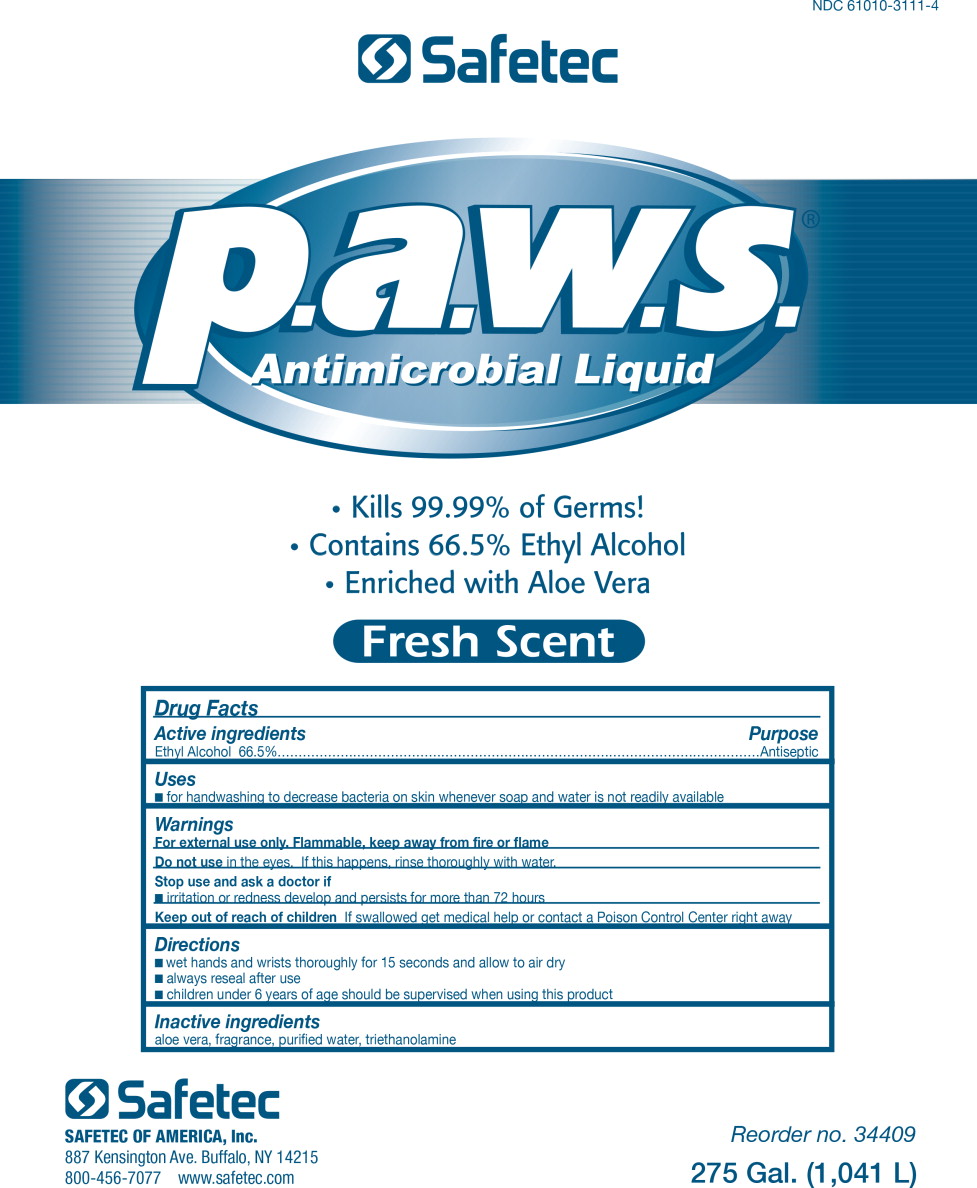 DRUG LABEL: Antimicrobial
NDC: 61010-3111 | Form: LIQUID
Manufacturer: Safetec of America, Inc.
Category: otc | Type: HUMAN OTC DRUG LABEL
Date: 20240205

ACTIVE INGREDIENTS: ALCOHOL 665 mL/1 L
INACTIVE INGREDIENTS: ALOE; WATER; TROLAMINE

Antimicrobial Liquid Paws

Drug Facts

Active ingredient

Ethyl Alcohol 66.5%

Purpose

Antiseptic

Uses

- for handwashing to decrease bacteria on skin whenever soap and water is not readily available

Warnings

For external use only. Flammable, keep away from fire or flame

DO NOT USE

Do not usein the eyes. If this happens, rinse thoroughly with water.

Stop use and ask doctor if

- irritation or redness develop and persists for more than 72 hours

Keep out of reach of children.If swallowed, get medical help or contact a Poison Control Center right away

Directions

- wet hands and wrists thoroughly for 15 seconds and allow to air dry
- always reseal after use
- children under 6 years of age should be supervised when using this product

Inactive ingredients

Aloe vera, fragrance, purified water, triethanolamine

SAFETEC OF AMERICA, Inc.
887 Kensington Ave. Buffalo, NY 14215
800-456-7077 www.safetec.com

Reorder no. 34409

275 Gal. (1,041 L)

PRINCIPAL DISPLAY PANEL – 275 Gallon Container Label

NDC 61010-3111-4

Safetec

p.a.w.s.

Antimicrobial

Liquid

- Kills 99.9% of Germs!
- Contains 66.5% Ethyl Alcohol
- Enriched with Aloe Vera

Fresh Scent

Drug Facts

Active Ingredient Purpose

Ethyl Alcohol 66.5% Antiseptic

Uses

- for handwashing to decrease bacteria on skin whenever soap and water is not readily available

Warnings

For external use only. Flammable, keep away from fire or flame

Do not usein the eyes. If this happens, rinse thoroughly with water.

Stop use and ask doctor if

- irritation or redness develop and persists for more than 72 hours

Keep out of reach of children.If swallowed, get medical help or contact a Poison Control Center right away

Directions

- wet hands and wrists thoroughly for 15 seconds and allow to air dry
- always reseal after use
- children under 6 years of age should be supervised when using this product

Inactive ingredients

Aloe vera, fragrance, purified water, triethanolamine

SAFETEC OF AMERICA, Inc.

887 Kensington Ave. Buffalo, NY 14215

800-456-7077 www.safetec.com

Reorder no. 34409

275 Gal. (1,041 L)